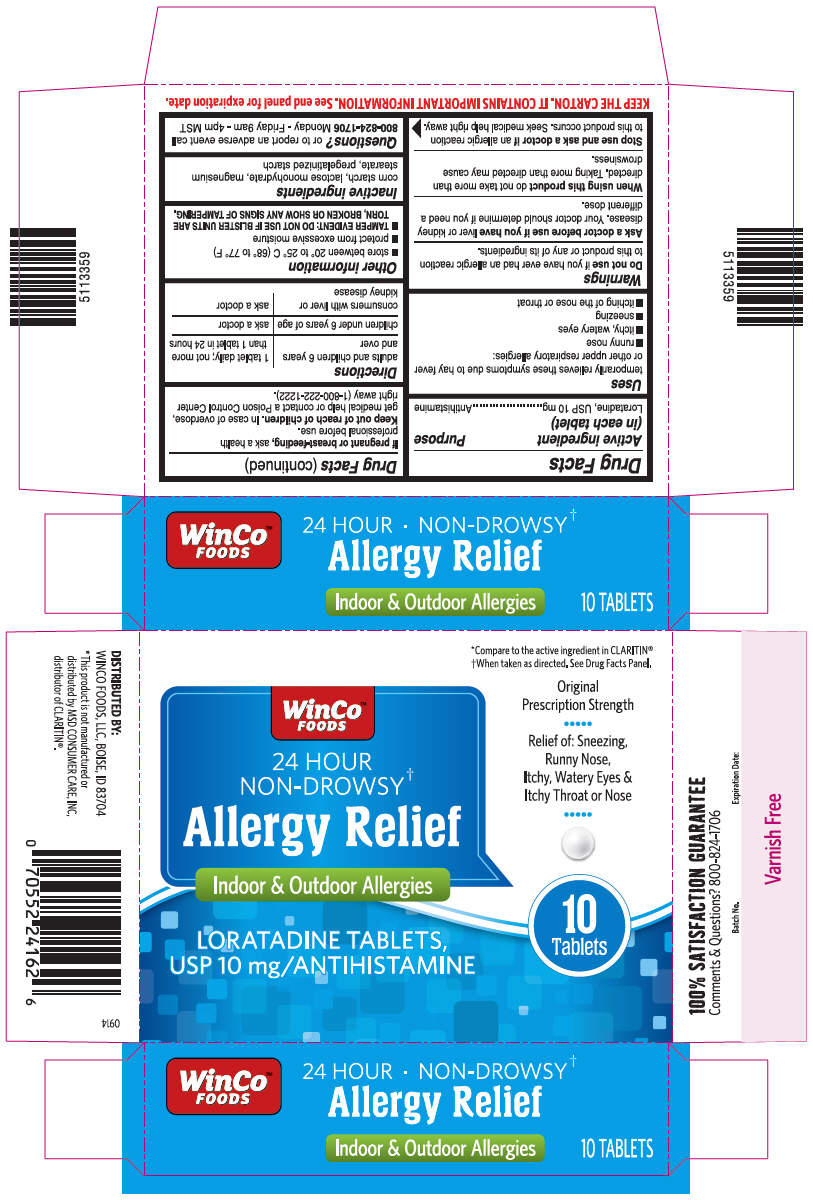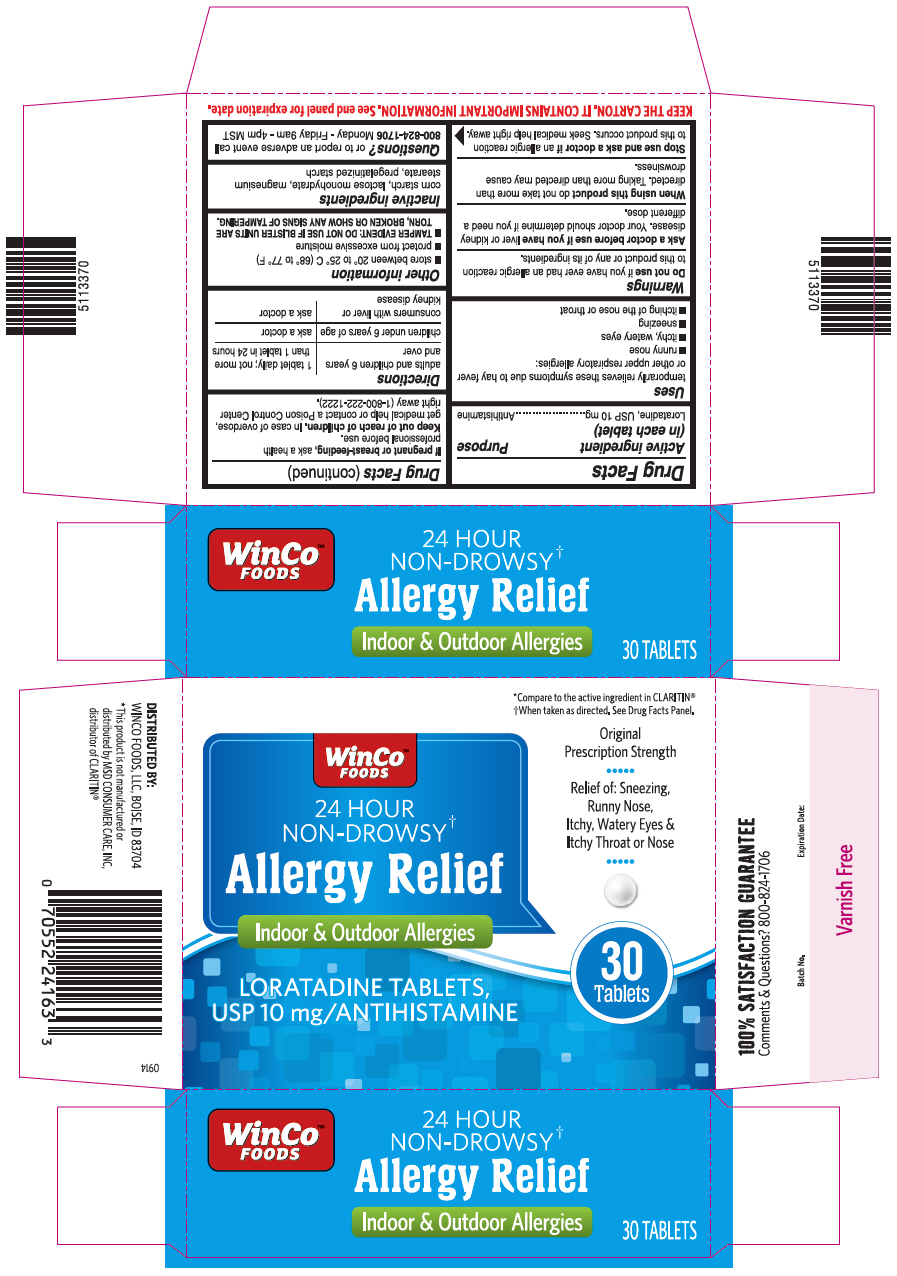 DRUG LABEL: Loratadine Allergy Relief
NDC: 67091-245 | Form: TABLET
Manufacturer: WinCo Foods, LLC
Category: otc | Type: HUMAN OTC DRUG LABEL
Date: 20180829

ACTIVE INGREDIENTS: LORATADINE 10 mg/1 1
INACTIVE INGREDIENTS: STARCH, CORN; LACTOSE MONOHYDRATE; MAGNESIUM STEARATE

Drug Facts

ACTIVE INGREDIENT(S)

Loratadine, USP 10 mg

PURPOSE

Antihistamine

USE(S)

Temporarily relieves these symptoms due to hay fever or other upper respiratory allergies:

- runny nose
- itchy, watery eyes
- sneezing
- itching of the nose or throat

WARNINGS

Do not use

If you have ever had an allergic reaction to this product or any of its ingredients.

Ask a doctor before use if you have

Liver or kidney disease. Your doctor should determine if you need a different dose.

When using this product

Do not take more than directed. Taking more than directed may cause drowsiness.

Stop use and ask a doctor if

an allergic reaction to this product occurs. Seek medical help right away.

If pregnant or breast-feeding,

Ask a health professional before use.

Keep out of reach of children.

In case of overdose, get medical help or contact a Poison Control Center right away (1-800-222-1222).

DIRECTIONS

adults and children 6 years and over | 1 tablet daily; not more than 1 tablet in 24 hours
children under 6 years of age | ask a doctor
consumers with liver and kidney disease | ask a doctor

OTHER INFORMATION

- store between 20° to 25° C (68° to 77° F)
- protect from excessive moisture
- TAMPER EVIDENT: DO NOT USE IF BLISTER UNITS ARE TORN, BROKEN OR SHOW AN SIGN OF TAMPERING.

INACTIVE INGREDIENTS

Corn starch, lactose monohydrate, magnesium stearate, pregelatinized starch

QUESTIONS?

or to report an adverse event call 800-824-7984 Monday - Friday 9am - 4pm MST

PRINCIPAL DISPLAY PANEL - 10 Tablet Blister Pack Carton

*Compare to the active ingredient in CLARITIN®
†When taken as directed. See Drug Facts Panel.

WinCo™
FOODS

24 HOUR
NON-DROWSY†

Allergy Relief

Indoor & Outdoor Allergies

LORATADINE TABLETS,
USP 10 mg/ANTIHISTAMINE

Original
Prescription Strength

Relief of: Sneezing,
Runny Nose,
Itchy, Watery Eyes &
Itchy Throat or Nose

10
Tablets

PRINCIPAL DISPLAY PANEL - 30 Tablet Blister Pack Carton

*Compare to the active ingredient in CLARITIN®
†When taken as directed. See Drug Facts Panel.

WinCo™
FOODS

24 HOUR
NON-DROWSY†

Allergy Relief

Indoor & Outdoor Allergies

LORATADINE TABLETS,
USP 10 mg/ANTIHISTAMINE

Original
Prescription Strength

Relief of: Sneezing,
Runny Nose,
Itchy, Watery Eyes &
Itchy Throat or Nose

30
Tablets